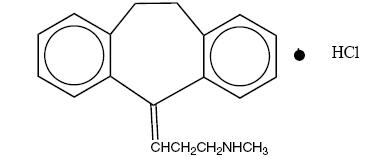 DRUG LABEL: Unknown
Manufacturer: Taro Pharmaceuticals U.S.A., Inc.
Category: prescription | Type: HUMAN PRESCRIPTION DRUG LABEL
Date: 20081104

Nortriptyline
Hydrochloride
Oral Solution, USP

Rx only

Suicidality and Antidepressant Drugs

Antidepressants increased the risk compared to placebo of suicidal thinking and behavior (suicidality) in children, adolescents, and young adults in short-term studies of major depressive disorder (MDD) and other psychiatric disorders. Anyone considering the use of nortriptyline hydrochloride oral solution or any other antidepressant in a child, adolescent, or young adult must balance this risk with the clinical need. Short-term studies did not show an increase in the risk of suicidality with antidepressants compared to placebo in adults beyond age 24; there was a reduction in risk with antidepressants compared to placebo in adults aged 65 and older. Depression and certain other psychiatric disorders are themselves associated with increases in the risk of suicide. Patients of all ages who are started on antidepressant therapy should be monitored appropriately and observed closely for clinical worsening, suicidality, or unusual changes in behavior. Families and caregivers should be advised of the need for close observation and communication with the prescriber. Nortriptyline hydrochloride is not approved for use in pediatric patients. (See Warnings: Clinical Worsening and Suicide Risk, Precautions: Information for Patients, and Precautions: Pediatric Use.)

DESCRIPTION

Nortriptyline Hydrochloride, USP is 1-propanamine, 3-(10, 11-dihydro-5H-dibenzo [a,d] cyclohepten-5-ylidene)-N-methyl, hydrochloride. Its molecular weight is 299.8, and its molecular formula is C19H21N•HCl.

The oral solution contains nortriptyline hydrochloride equivalent to 10 mg/5 mL (38.0 µmol) of the base and 4% alcohol (v/v). It also contains benzoic acid, cherry flavor (artificial), sorbitol solution 70%, and purified water.

The structural formula is as follows:

ACTIONS

The mood elevating mechanism of tricyclic antidepressants is at present unknown. Nortriptyline hydrochloride is not a monoamine oxidase inhibitor. It inhibits the activity of such diverse agents as histamine, 5-hydroxytryptamine, and acetylcholine. It increases the pressor effect of norepinephrine but blocks the pressor response of phenethylamine. Studies suggest that nortriptyline hydrochloride interferes with the transport, release, and storage of catecholamines. Operant conditioning techniques in rats and pigeons suggest that nortriptyline hydrochloride has a combination of stimulant and depressant properties.

INDICATIONS

Nortriptyline hydrochloride is indicated for the relief of symptoms of depression.

Endogenous depressions are more likely to be alleviated than are other depressive states.

CONTRAINDICATIONS

The concurrent use of nortriptyline hydrochloride or other tricyclic antidepressants with a monoamine oxidase (MAO) inhibitor is contraindicated. Hyperpyretic crises, severe convulsions, and fatalities have occurred when similar tricyclic antidepressants were used in such combinations. It is advisable to discontinue the MAO inhibitor at least 2 weeks before treatment with nortriptyline hydrochloride is to be started.

Patients hypersensitive to nortriptyline hydrochloride should not be given the drug. Cross-sensitivity between nortriptyline hydrochloride and other dibenzazepines is a possibility.

Nortriptyline hydrochloride is contraindicated during the acute recovery period after myocardial infarction.

WARNINGS

Clinical Worsening and Suicide Risk

Patients with major depressive disorder (MDD), both adult and pediatric, may experience worsening of their depression and/or the emergence of suicidal ideation and behavior (suicidality) or unusual changes in behavior, whether or not they are taking antidepressant medications, and this risk may persist until significant remission occurs. Suicide is a known risk of depression and certain other psychiatric disorders, and these disorders themselves are the strongest predictors of suicide. There has been a long-standing concern, however, that antidepressants may have a role in inducing worsening of depression and the emergence of suicidality in certain patients during the early phases of treatment. Pooled analyses of short-term placebo-controlled trials of antidepressant drugs (SSRIs and others) showed that these drugs increase the risk of suicidal thinking and behavior (suicidality) in children, adolescents, and young adults (ages 18-24) with major depressive disorder (MDD) and other psychiatric disorders. Short-term studies did not show an increase in the risk of suicidality with antidepressants compared to placebo in adults beyond age 24; there was a reduction with antidepressants compared to placebo in adults aged 65 and older.

The pooled analyses of placebo-controlled trials in children and adolescents with MDD, obsessive compulsive disorder (OCD), or other psychiatric disorders included a total of 24 short-term trials of 9 antidepressant drugs in over 4400 patients. The pooled analyses of placebo-controlled trials in adults with MDD or other psychiatric disorders included a total of 295 short-term trials (median duration of 2 months) of 11 antidepressant drugs in over 77,000 patients. There was considerable variation in risk of suicidality among drugs, but a tendency toward an increase in the younger patients for almost all drugs studied. There were differences in absolute risk of suicidality across the different indications, with the highest incidence in MDD. The risk differences (drug vs placebo), however, were relatively stable within age strata and across indications. These risk differences (drug-placebo difference in the number of cases of suicidality per 1000 patients treated) are provided in Table 1.

Table 1
Age Range | Drug-Placebo Difference in Number of Cases of Suicidality per 1000 Patients Treated
 | Increases Compared to Placebo
<18 | 14 additional cases
18-24 | 5 additional cases
 | Decreases Compared to Placebo
25-64 | 1 fewer case
>65 | 6 fewer cases

No suicides occurred in any of the pediatric trials. There were suicides in the adult trials, but the number was not sufficient to reach any conclusion about drug effect on suicide.

It is unknown whether the suicidality risk extends to longer-term use, i.e., beyond several months. However, there is substantial evidence from placebo-controlled maintenance trials in adults with depression that the use of antidepressants can delay the recurrence of depression.

All patients being treated with antidepressants for any indication should be monitored appropriately and observed closely for clinical worsening, suicidality, and unusual changes in behavior, especially during the initial few months of a course of drug therapy, or at times of dose changes, either increases or decreases.

The following symptoms, anxiety, agitation, panic attacks, insomnia, irritability, hostility, aggressiveness, impulsivity, akathisia (psychomotor restlessness), hypomania, and mania, have been reported in adult and pediatric patients being treated with antidepressants for major depressive disorder as well as for other indications, both psychiatric and nonpsychiatric. Although a causal link between the emergence of such symptoms and either the worsening of depression and/or the emergence of suicidal impulses has not been established, there is concern that such symptoms may represent precursors to emerging suicidality.

Consideration should be given to changing the therapeutic regimen, including possibly discontinuing the medication, in patients whose depression is persistently worse, or who are experiencing emergent suicidality or symptoms that might be precursors to worsening depression or suicidality, especially if these symptoms are severe, abrupt in onset, or were not part of the patient's presenting symptoms.

Families and caregivers of patients being treated with antidepressants for major depressive disorder or other indications, both psychiatric and nonpsychiatric, should be alerted about the need to monitor patients for the emergence of agitation, irritability, unusual changes in behavior, and the other symptoms described above, as well as the emergence of suicidality, and to report such symptoms immediately to health care providers. Such monitoring should include daily observation by families and caregivers. Prescriptions for nortriptyline hydrochloride oral solution should be written for the smallest quantity consistent with good patient management, in order to reduce the risk of overdose.

Screening Patients for Bipolar Disorder

A major depressive episode may be the initial presentation of bipolar disorder. It is generally believed (though not established in controlled trials) that treating such an episode with an antidepressant alone may increase the likelihood of precipitation of a mixed/manic episode in patients at risk for bipolar disorder. Whether any of the symptoms described above represent such a conversion is unknown. However, prior to initiating treatment with an antidepressant, patients with depressive symptoms should be adequately screened to determine if they are at risk for bipolar disorder; such screening should include a detailed psychiatric history, including a family history of suicide, bipolar disorder, and depression. It should be noted that nortriptyline hydrochloride is not approved for use in treating bipolar depression.

Patients with cardiovascular disease should be given nortriptyline hydrochloride only under close supervision because of the tendency of the drug to produce sinus tachycardia and to prolong the conduction time. Myocardial infarction, arrhythmia, and strokes have occurred. The antihypertensive action of guanethidine and similar agents may be blocked. Because of its anticholinergic activity, nortriptyline hydrochloride should be used with great caution in patients who have glaucoma or a history of urinary retention. Patients with a history of seizures should be followed closely when nortriptyline hydrochloride is administered, because this drug is known to lower the convulsive threshold. Great care is required if nortriptyline hydrochloride is given to hyperthyroid patients or to those receiving thyroid medication, because cardiac arrhythmias may develop.

Nortriptyline hydrochloride may impair the mental and/or physical abilities required for the performance of hazardous tasks, such as operating machinery or driving a car; therefore, the patient should be warned accordingly.

Excessive consumption of alcohol in combination with nortriptyline therapy may have a potentiating effect, which may lead to the danger of increased suicidal attempts or overdosage, especially in patients with histories of emotional disturbances or suicidal ideation.

Use in Pregnancy

Safe use of nortriptyline hydrochloride during pregnancy and lactation has not been established; therefore, when the drug is administered to pregnant patients, nursing mothers, or women of childbearing potential, the potential benefits must be weighed against the possible hazards. Animal reproduction studies have yielded inconclusive results.

PRECAUTIONS

Information for Patients

Prescribers or other health professionals should inform patients, their families, and their caregivers about the benefits and risks associated with treatment with nortriptyline hydrochloride and should counsel them in its appropriate use. A patient Medication Guide about Antidepressant Medicines, Depression and other Serious Mental Illness, and Suicidal Thoughts or Actions is available for nortriptyline hydrochloride. The prescriber or health professional should instruct patients and their caregivers to read the Medication Guide and should assist them in understanding its contents. Patients should be given the opportunity to discuss the contents of the Medication Guide and to obtain answers to any questions they may have. The complete text of the Medication Guide is reprinted at the end of this document.

Patients should be advised of the following issues and asked to alert their prescriber if these occur while taking nortriptyline hydrochloride.

Clinical Worsening and Suicide Risk

Patients, their families, and their caregivers should be encouraged to be alert to the emergence of anxiety, agitation, panic attacks, insomnia, irritability, hostility, aggressiveness, impulsivity, akathisia (psychomotor restlessness), hypomania, mania, other unusual changes in behavior, worsening of depression, and suicidal ideation, especially early during antidepressant treatment and when the dose is adjusted up or down. Families and caregivers of patients should be advised to look for the emergence of such symptoms on a day-to-day basis, since changes may be abrupt. Such symptoms should be reported to the patient's prescriber or health professional, especially if they are severe, abrupt in onset, or were not part of the patient's presenting symptoms. Symptoms such as these may be associated with an increased risk for suicidal thinking and behavior and indicate a need for very close monitoring and possibly changes in the medication.

Pediatric Use

Safety and effectiveness in the pediatric population have not been established (see BOX WARNING and WARNINGS—Clinical Worsening and Suicide Risk).

Anyone considering the use of nortriptyline hydrochloride in a child or adolescent must balance the potential risks with the clinical need.

General

The use of nortriptyline hydrochloride in schizophrenic patients may result in exacerbation of the psychosis or may activate latent schizophrenic symptoms. If the drug is given to overactive or agitated patients, increased anxiety and agitation may occur. In manic-depressive patients, nortriptyline hydrochloride may cause symptoms of the manic phase to emerge.

Troublesome patient hostility may be aroused by the use of nortriptyline hydrochloride. As may happen with other drugs of its class, epileptiform seizures may accompany its administration.

When it is essential, the drug may be administered concurrently with electroconvulsive therapy, although the hazards may be increased. Discontinue the drug for several days, if possible, prior to elective surgery.

The possibility of a suicidal attempt by a depressed patient remains after the initiation of treatment; in this regard, it is important that the least possible quantity of drug be dispensed at any given time.

Both elevation and lowering of blood sugar levels have been reported.

A case of significant hypoglycemia has been reported after the addition of nortriptyline (125 mg/day) in a type II diabetic patient maintained on chlorpropamide (250 mg/day).

Drug Interactions

Steady-state serum concentrations of tricyclic antidepressants are reported to fluctuate significantly when cimetidine is either added or deleted from the drug regimen. Serious anticholinergic symptoms (severe dry mouth, urinary retention, blurred vision) have been associated with elevations in the serum levels of tricyclic antidepressants when cimetidine is added to the drug regimen. In addition, higher-than expected steady-state serum concentrations of tricyclic antidepressants have been observed when therapy is initiated in patients already taking cimetidine.

In well-controlled patients undergoing concurrent therapy with cimetidine, a decrease in the steady-state serum concentrations of tricyclic antidepressants may occur when cimetidine therapy is discontinued. The therapeutic efficacy of tricyclic antidepressants may be compromised in these patients when cimetidine is discontinued. Several of the tricyclic antidepressants have been cited in these reports.

There have been greater than 2-fold increases in previously stable plasma levels of other antidepressants, including nortriptyline, when fluoxetine hydrochloride has been administered in combination with these agents. Fluoxetine and its active metabolite, norfluoxetine, have long half-lives (4 to 16 days for norfluoxetine), that may affect strategies during conversion from one drug to the other.

Administration of reserpine during therapy with a tricyclic antidepressant has been shown to produce a "stimulating" effect in some depressed patients.

Close supervision and careful adjustment of the dosage are required when nortriptyline hydrochloride is used with other anticholinergic drugs or sympathomimetic drugs. The patient should be informed that the response to alcohol may be exaggerated.

Drugs Metabolized by P450IID6

A subset (3% to 10%) of the population has reduced activity of certain drug metabolizing enzymes such as the cytochrome P450 isoenzyme P450IID6. Such individuals are referred to as "poor metabolizers" of drugs such as debrisoquin, dextromethorphan, and the tricyclic antidepressants. These individuals may have higher than expected plasma concentrations of tricyclic antidepressants when given usual doses. In addition, certain drugs that are metabolized by this isoenzyme, including many antidepressants (tricyclic antidepressants, selective serotonin reuptake inhibitors, and others), may inhibit the activity of this isoenzyme, and thus may make normal metabolizers resemble poor metabolizers with regard to concomitant therapy with other drugs metabolized by this enzyme system, leading to drug interactions.

Concomitant use of tricyclic antidepressants with other drugs metabolized by cytochrome P450IID6 may require lower doses than usually prescribed for either the tricyclic antidepressant or the other drug. Therefore, co-administration of tricyclic antidepressants with other drugs that are metabolized by this isoenzyme, including other antidepressants, phenothiazines, carbamazepine, and Type 1C antiarrhythmics (eg, propafenone, flecainide, and encainide), or that inhibit this enzyme (eg, quinidine), should be approached with caution.

Geriatric Use

Confusional states following tricyclic antidepressant administration have been reported in the elderly (see ADVERSE REACTIONS). Higher plasma concentrations of the active nortriptyline metabolite, 10-hydroxynortriptyline, have also been reported in elderly patients (see Plasma Levels under DOSAGE AND ADMINISTRATION). Lower than usual dosages are recommended for the elderly patients (see Elderly Patients under DOSAGE AND ADMINISTRATION).

ADVERSE REACTIONS

NOTE: Included in the following list are a few adverse reactions that have not been reported with this specific drug. However, the pharmacologic similarities among the tricyclic antidepressant drugs require that each of these reactions be considered when nortriptyline is administered.

Cardiovascular—Hypotension, hypertension, tachycardia, palpitation, myocardial infarction, arrhythmias, heart block, stroke.

Psychiatric—Confusional states (especially in the elderly), with hallucinations, disorientation, delusions; anxiety, restlessness, agitation; insomnia, panic, nightmares; hypomania; exacerbation of psychosis.

Neurologic—Numbness, tingling, paresthesias of extremities; incoordination, ataxia, tremors; peripheral neuropathy; extrapyramidal symptoms; seizures, alteration of EEG patterns; tinnitus.

Anticholinergic—Dry mouth and, rarely, associated sublingual adenitis or gingivitis; blurred vision, disturbance of accommodation, mydriasis; constipation, paralytic ileus; urinary retention, delayed micturition, dilation of the urinary tract.

Allergic—Skin rash, petechiae, urticaria, itching, photosensitization (avoid excessive exposure to sunlight); edema (general or of face and tongue), drug fever, cross-sensitivity with other tricyclic drugs.

Hematologic—Bone-marrow depression, including agranulocytosis; aplastic anemia; eosinophilia; purpura; thrombocytopenia.

Gastrointestinal—Nausea and vomiting, anorexia, epigastric distress, diarrhea; peculiar taste, stomatitis, abdominal cramps, black tongue, constipation, paralytic ileus.

Endocrine—Gynecomastia in the male; breast enlargement and galactorrhea in the female; increased or decreased libido, impotence; testicular swelling; elevation or depression of blood sugar levels; syndrome of inappropriate ADH (antidiuretic hormone) secretion.

Other—Jaundice (simulating obstructive); altered liver function, hepatitis, and liver necrosis; weight gain or loss; perspiration; flushing; urinary frequency, nocturia; drowsiness, dizziness, weakness, fatigue; headache; parotid swelling; alopecia.

Withdrawal Symptoms—Though these are not indicative of addiction, abrupt cessation of treatment after prolonged therapy may produce nausea, headache, and malaise.

OVERDOSAGE

Deaths may occur from overdosage with this class of drugs. Multiple drug ingestion (including alcohol) is common in deliberate tricyclic antidepressant overdose. As the management is complex and changing, it is recommended that the physician contact a poison control center for current information on treatment. Signs and symptoms of toxicity develop rapidly after tricyclic antidepressant overdose; therefore, hospital monitoring is required as soon as possible.

Manifestations

Critical manifestations of overdose include: cardiac dysrhythmias, severe hypotension, convulsions, and CNS depression, including coma. Changes in the electrocardiogram, particularly in QRS axis or width, are clinically significant indicators of tricyclic antidepressant toxicity.

Other signs of overdose may include: confusion, disturbed concentration, transient visual hallucinations, dilated pupils, agitation, hyperactive reflexes, stupor, drowsiness, muscle rigidity, vomiting, hypothermia, hyperpyrexia, or many of the symptoms listed under ADVERSE REACTIONS.

Management

General

Obtain an ECG and immediately initiate cardiac monitoring. Protect the patient's airway, establish an intravenous line and initiate gastric decontamination.

A minimum of six hours of observation with cardiac monitoring and observation for signs of CNS or respiratory depression, hypotension, cardiac dysrhythmias and/or conduction blocks, and seizures is necessary. If signs of toxicity occur at any time during this period, extended monitoring is required. There are case reports of patients succumbing to fatal dysrhythmias late after overdose; these patients had clinical evidence of significant poisoning prior to death and most received inadequate gastrointestinal decontamination. Monitoring of plasma drug levels should not guide management of the patient.

Gastrointestinal Decontamination

All patients suspected of tricyclic antidepressant overdose should receive gastrointestinal decontamination. This should include large volume gastric lavage followed by activated charcoal. If consciousness is impaired, the airway should be secured prior to lavage. Emesis is contraindicated.

Cardiovascular

A maximal limb-lead QRS duration of ≥ 0.10 seconds may be the best indication of the severity of the overdose. Intravenous sodium bicarbonate should be used to maintain the serum pH in the range of 7.45 to 7.55. If the pH response is inadequate, hyperventilation may also be used. Concomitant use of hyperventilation and sodium bicarbonate should be done with extreme caution, with frequent pH monitoring. A pH > 7.60 or a pCO2 < 20 mm Hg is undesirable. Dysrhythmias unresponsive to sodium bicarbonate therapy/hyperventilation may respond to lidocaine, bretylium or phenytoin. Type 1A and 1C antiarrhythmics are generally contraindicated (eg, quinidine, disopyramide, and procainamide).

In rare instances, hemoperfusion may be beneficial in acute refractory cardiovascular instability in patients with acute toxicity. However, hemodialysis, peritoneal dialysis, exchange transfusions, and forced diuresis generally have been reported as ineffective in tricyclic antidepressant poisoning.

CNS

In patients with CNS depression, early intubation is advised because of the potential for abrupt deterioration. Seizures should be controlled with benzodiazepines, or if these are ineffective, other anticonvulsants (eg, phenobarbital, phenytoin). Physostigmine is not recommended except to treat life-threatening symptoms that have been unresponsive to other therapies, and then only in consultation with a poison control center.

Psychiatric Follow-up

Since overdosage is often deliberate, patients may attempt suicide by other means during the recovery phase. Psychiatric referral may be appropriate.

Pediatric Management

The principles of management of pediatric and adult overdosages are similar. It is strongly recommended that the physician contact the local poison control center for specific pediatric treatment.

DOSAGE AND ADMINISTRATION

Nortriptyline hydrochloride is not recommended for pediatric patients. Nortriptyline hydrochloride is administered orally in the form of an oral solution. Lower than usual dosages are recommended for elderly patients. The use of lower dosages for outpatients is more important than for hospitalized patients who will be treated under close supervision. The physician should initiate dosage at a low level and increase it gradually, checking the clinical response carefully and noting any evidence of intolerance. Following remission, maintenance medication may be required for a longer period of time at the lowest dose that will maintain remission.

If a patient develops minor side effects, the dosage should be reduced. The drug should be discontinued promptly if adverse effects of a serious nature or allergic manifestations occur.

Usual Adult Dose

25 mg 3 or 4 times daily; dosage should begin at a low level and be increased as required. As an alternate regimen, the total daily dose may be given once a day. When doses above 100 mg daily are administered, plasma levels of nortriptyline should be monitored and maintained in the optimum range of 50 to 150 ng/mL. Doses above 150 mg per day are not recommended.

Elderly Patients

30 to 50 mg/day in divided doses.

Plasma Levels

Optimal responses to nortriptyline have been associated with plasma concentrations of 50 to 150 ng/mL. Higher concentrations may be associated with more adverse experiences. Plasma concentrations are difficult to measure, and physicians should consult with the laboratory professional staff.

Larger plasma concentrations of the active nortriptyline metabolite 10-hydroxy nortriptyline have been reported in older patients. In one case, such a condition was associated with apparent cardiotoxicity despite the fact that nortriptyline concentrations were within the "therapeutic range." Clinical findings should predominate over plasma concentrations as primary determinants of dosage changes.

HOW SUPPLIED

Nortriptyline Hydrochloride Oral Solution USP, Equivalent to 10 mg/5 mL base is available in a 16 fl oz (473 mL) bottle…………………........NDC 51672-4119-9

STORAGE AND HANDLING

Store at 20°-25°C (68°-77°F) with excursions permitted between 15°-30°C (59°-86°F) [See USP Controlled Room Temperature]. Protect from light. Keep container tightly closed.

Mfd. by: Taro Pharmaceutical Industries Ltd., Haifa Bay, Israel 26110
Dist. by: Taro Pharmaceuticals U.S.A., Inc., Hawthorne, NY 10532

Issued: October, 2008

SPL SUPPLEMENTAL PATIENT MATERIAL

Medication Guide

Antidepressant Medicines, Depression and other Serious Mental Illness, and Suicidal Thoughts or Actions

Read the Medication Guide that comes with you or your family member's antidepressant medicine. This Medication Guide is only about the risk of suicidal thoughts and actions with antidepressant medicines. Talk to your, or your family member's, healthcare provider about:

- all risks and benefits of treatment with antidepressant medicines
- all treatment choices for depression or other serious mental illness

What is the most important information I should know about antidepressant medicines, depression and other serious mental illnesses, and suicidal thoughts or actions?

1. Antidepressant medicines may increase suicidal thoughts or actions in some children, teenagers, and young adults within the first few months of treatment.
2. Depression and other serious mental illnesses are the most important causes of suicidal thoughts and actions. Some people may have a particularly high risk of having suicidal thoughts or actions. These include people who have (or have a family history of) bipolar illness (also called manic-depressive illness) or suicidal thoughts or actions.
3. How can I watch for and try to prevent suicidal thoughts and actions in myself or a family member?
  - Pay close attention to any changes, especially sudden changes, in mood, behaviors, thoughts, or feelings. This is very important when an antidepressant medicine is started or when the dose is changed.
  - Call the healthcare provider right away to report new or sudden changes in mood, behavior, thoughts, or feelings.
  - Keep all follow-up visits with the healthcare provider as scheduled. Call the healthcare provider between visits as needed, especially if you have concerns about symptoms.

Call a healthcare provider right away if you or your family member has any of the following symptoms, especially if they are new, worse, or worry you:

- thoughts about suicide or dying
- attempts to commit suicide
- new or worse depression
- new or worse anxiety
- feeling very agitated or restless
- panic attacks
- trouble sleeping (insomnia)
- new or worse irritability
- acting aggressive, being angry, or violent
- acting on dangerous impulses
- an extreme increase in activity and talking (mania)
- other unusual changes in behavior or mood

What else do I need to know about antidepressant medicines?

- Never stop an antidepressant medicine without first talking to a health care provider. Stopping an antidepressant medicine suddenly can cause other symptoms.
- Antidepressants are medicines used to treat depression and other illnesses. It is important to discuss all the risks of treating depression and also the risks of not treating it. Patients and their families or other caregivers should discuss all treatment choices with the healthcare provider, not just the use of antidepressants.
- Antidepressant medicines have other side effects. Talk to the healthcare provider about the side effects of the medicine prescribed for you or your family member.
- Antidepressant medicines can interact with other medicines. Know all of the medicines that you or your family member takes. Keep a list of all medicines to show the healthcare provider. Do not start new medicines without first checking with your healthcare provider.
- Not all antidepressant medicines prescribed for children are FDA approved for use in children. Talk to your child's healthcare provider for more information.

This Medication Guide has been approved by the U.S. Food and Drug Administration for all antidepressants.

Mfd. by: Taro Pharmaceutical Industries Ltd., Haifa Bay, Israel 26110
Dist. by: Taro Pharmaceuticals U.S.A., Inc., Hawthorne, NY 10532

Issued: October, 2008